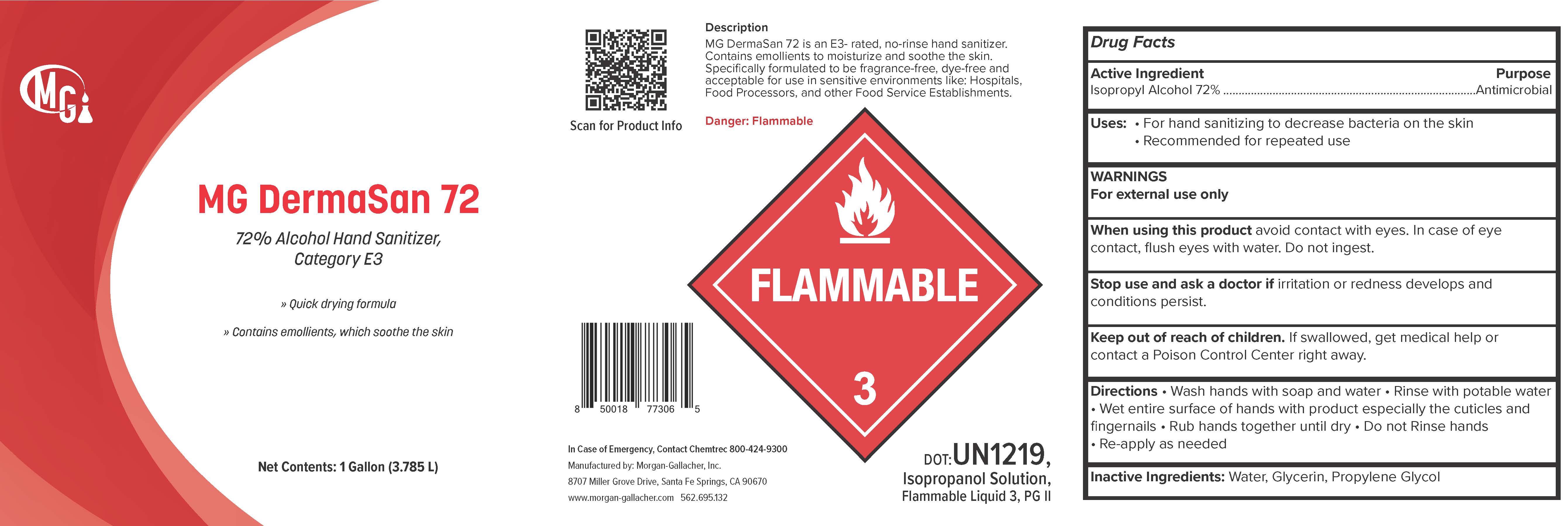 DRUG LABEL: MG DermaSan 72
NDC: 50241-330 | Form: GEL
Manufacturer: Morgan Gallacher Inc. DBA Custom Chemical Formulators Inc.
Category: otc | Type: HUMAN OTC DRUG LABEL
Date: 20251223

ACTIVE INGREDIENTS: ISOPROPYL ALCOHOL 0.72 L/1 L
INACTIVE INGREDIENTS: WATER; TRIISOPROPANOLAMINE; GLYCERIN; PROPYLENE GLYCOL

MG DermaSan72

Active Ingredient

Isopropyl Alcohol....72%

Purpose

Antimicrobial

Uses

- For hand sanitizing to decrease bacteria on the skin

Warnings

- For external use only.
- Flammable keep away from fire or flame

When using this product

- Avoid contact with eyes. In case of eye contract, flush eyes with water.

Stop use and ask doctor if

- irritation or redness develops, if condition persists for more than 72 hours.

Keep out of reach of children

If swallowed, get medical help or contact a Poison Conrol Center right away

Directions

- Place a small amount of MG DermaSan 72 in your palm to throughly cover your hands.
- Rub hands together briskly until dry.
- For children under 6 years of age should be supervised when using this product.

Inactive Ingredients

- Water
- Glycerin
- Propylene Glycol